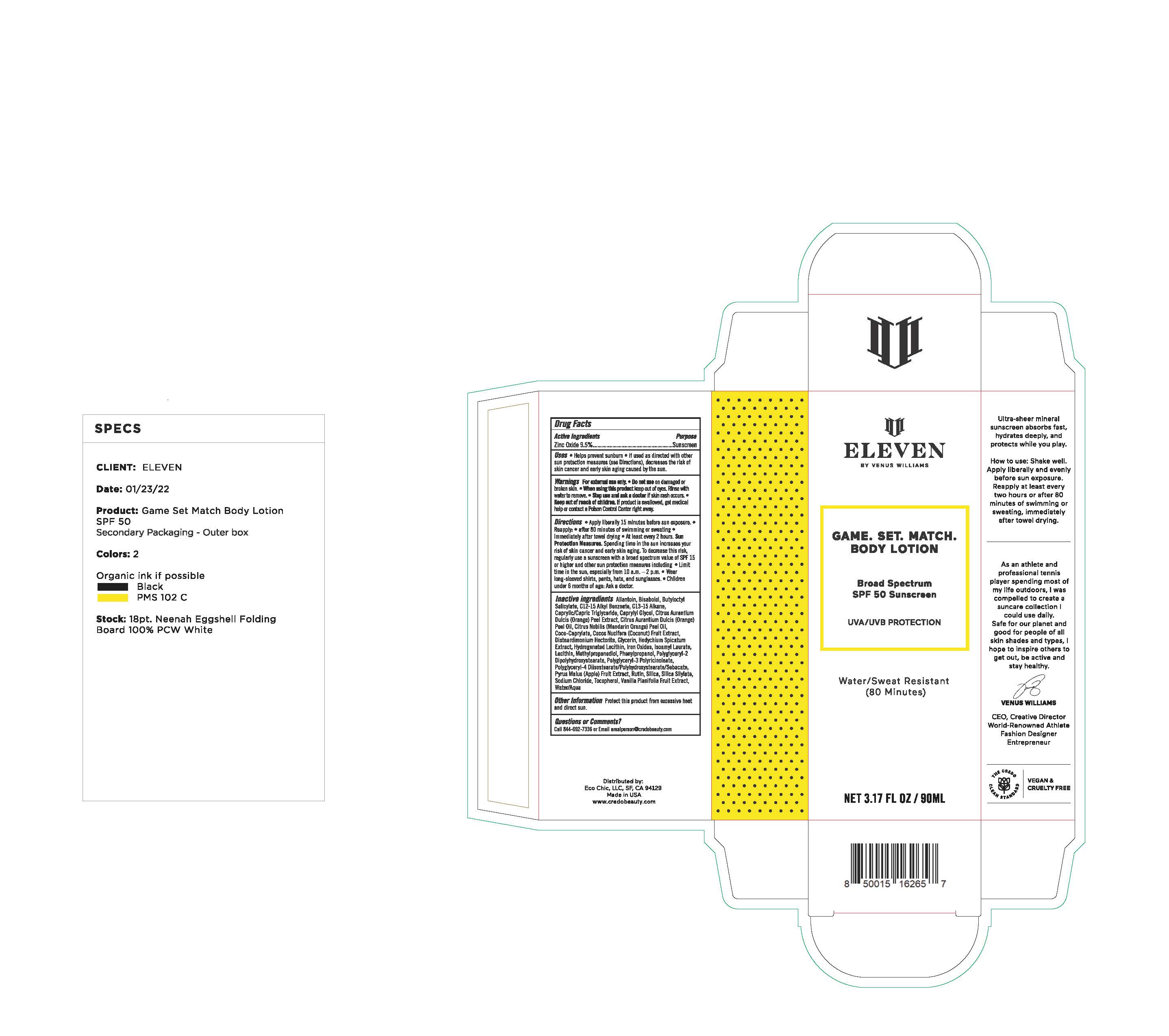 DRUG LABEL: ELEVEN BY VENUS WILLIAMS GAME SET MATCH BODY
NDC: 79163-347 | Form: LOTION
Manufacturer: Eco-Chic LLC
Category: otc | Type: HUMAN OTC DRUG LABEL
Date: 20251016

ACTIVE INGREDIENTS: ZINC OXIDE 105 mg/1 mL
INACTIVE INGREDIENTS: BUTYLOCTYL SALICYLATE; DISTEARDIMONIUM HECTORITE; RUTIN; GLYCERIN; ISOAMYL LAURATE; FERRIC OXIDE YELLOW; SILICON DIOXIDE; TOCOPHEROL; CAPRYLYL GLYCOL; COCO-CAPRYLATE; PHENYLPROPANOL; LECITHIN, SOYBEAN; METHYLPROPANEDIOL; POLYGLYCERYL-2 DIPOLYHYDROXYSTEARATE; ALLANTOIN; ALKYL (C12-15) BENZOATE; .ALPHA.-BISABOLOL, (+)-; WATER; SODIUM CHLORIDE; HYDROGENATED SOYBEAN LECITHIN; FERRIC OXIDE RED; FERROSOFERRIC OXIDE; POLYGLYCERYL-4 DIISOSTEARATE/POLYHYDROXYSTEARATE/SEBACATE; C13-15 ALKANE; POLYGLYCERYL-3 RICINOLEATE

ELEVEN BY VENUS WILLIAMS GAME SET MATCH BODY